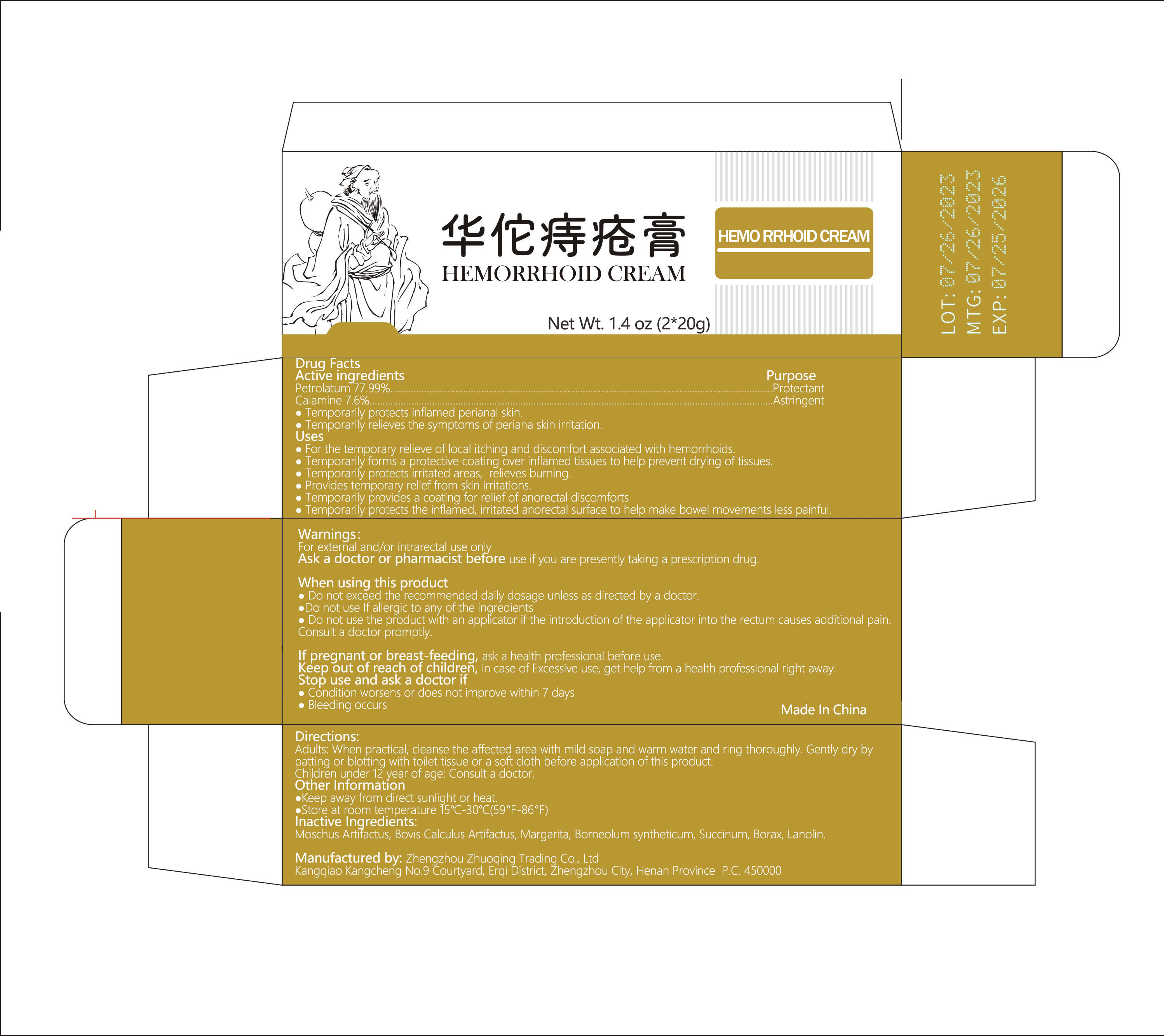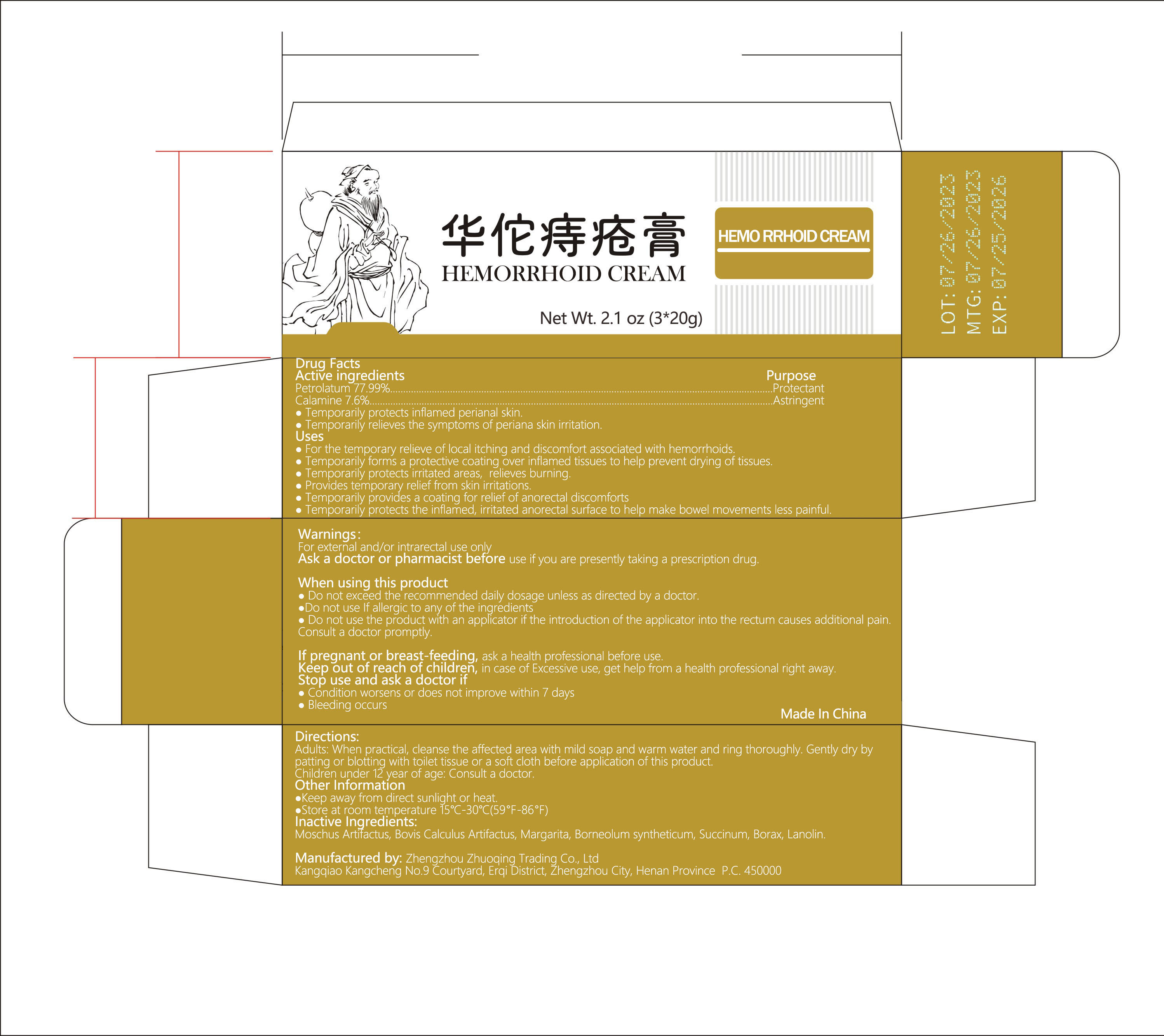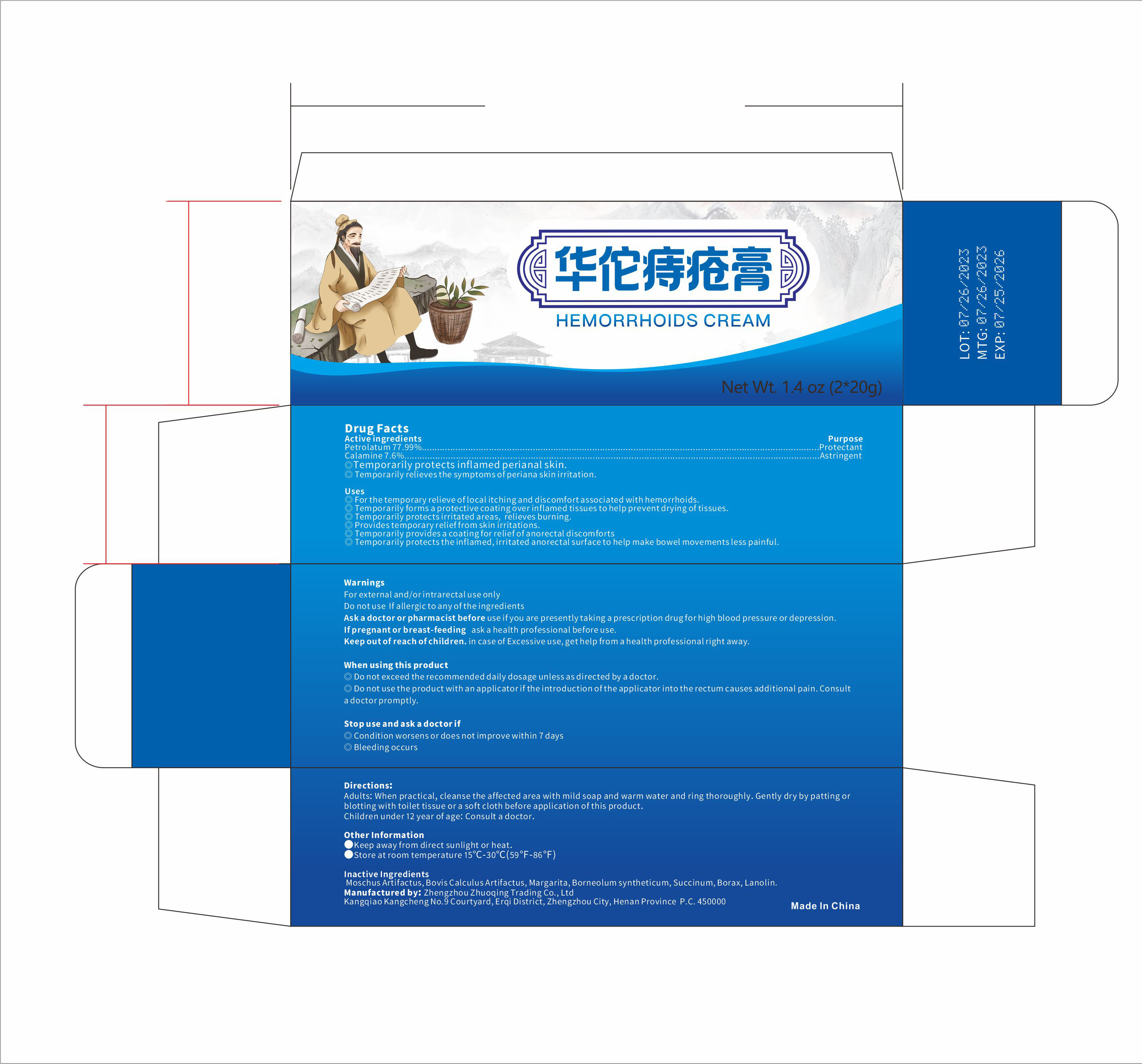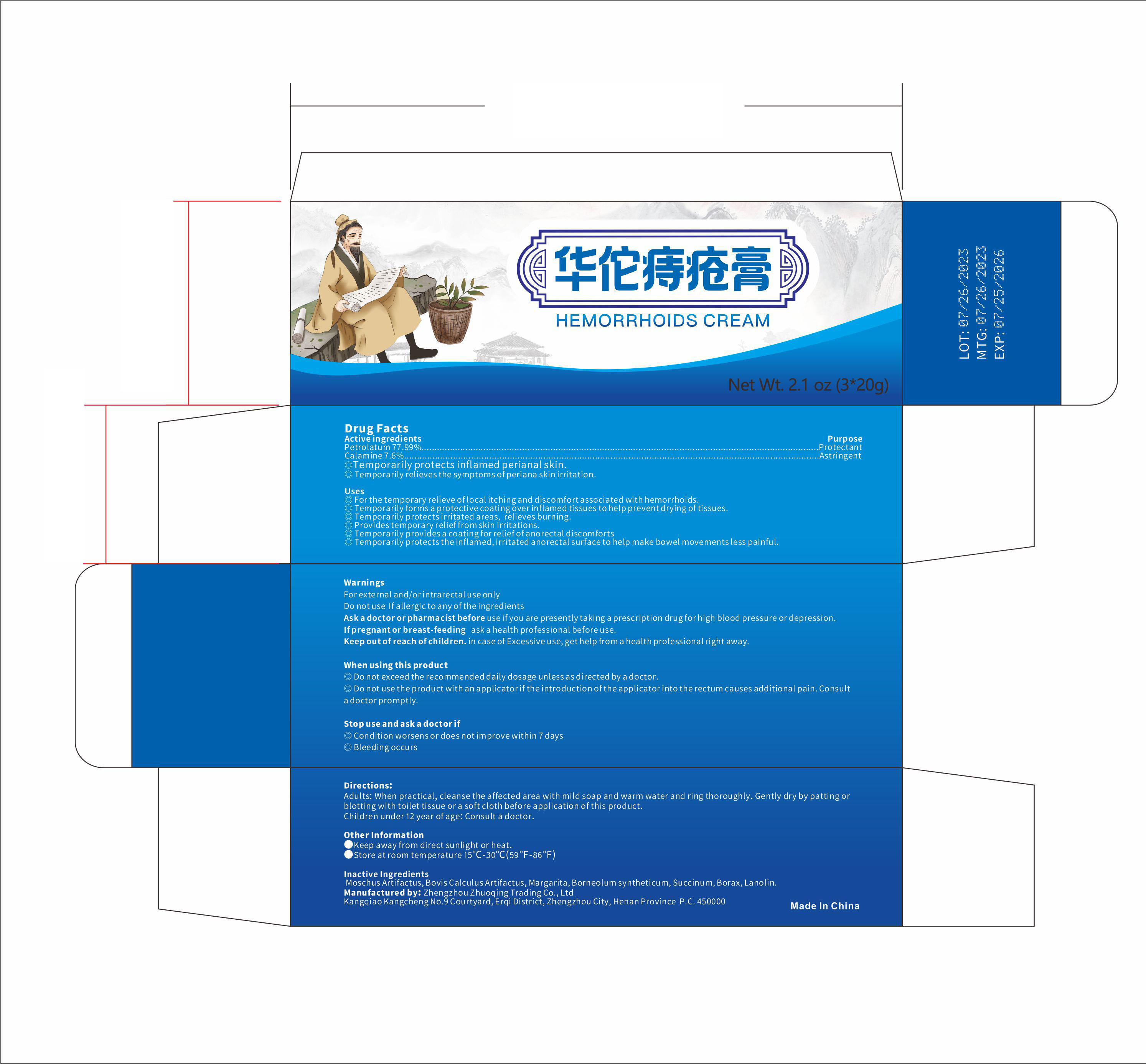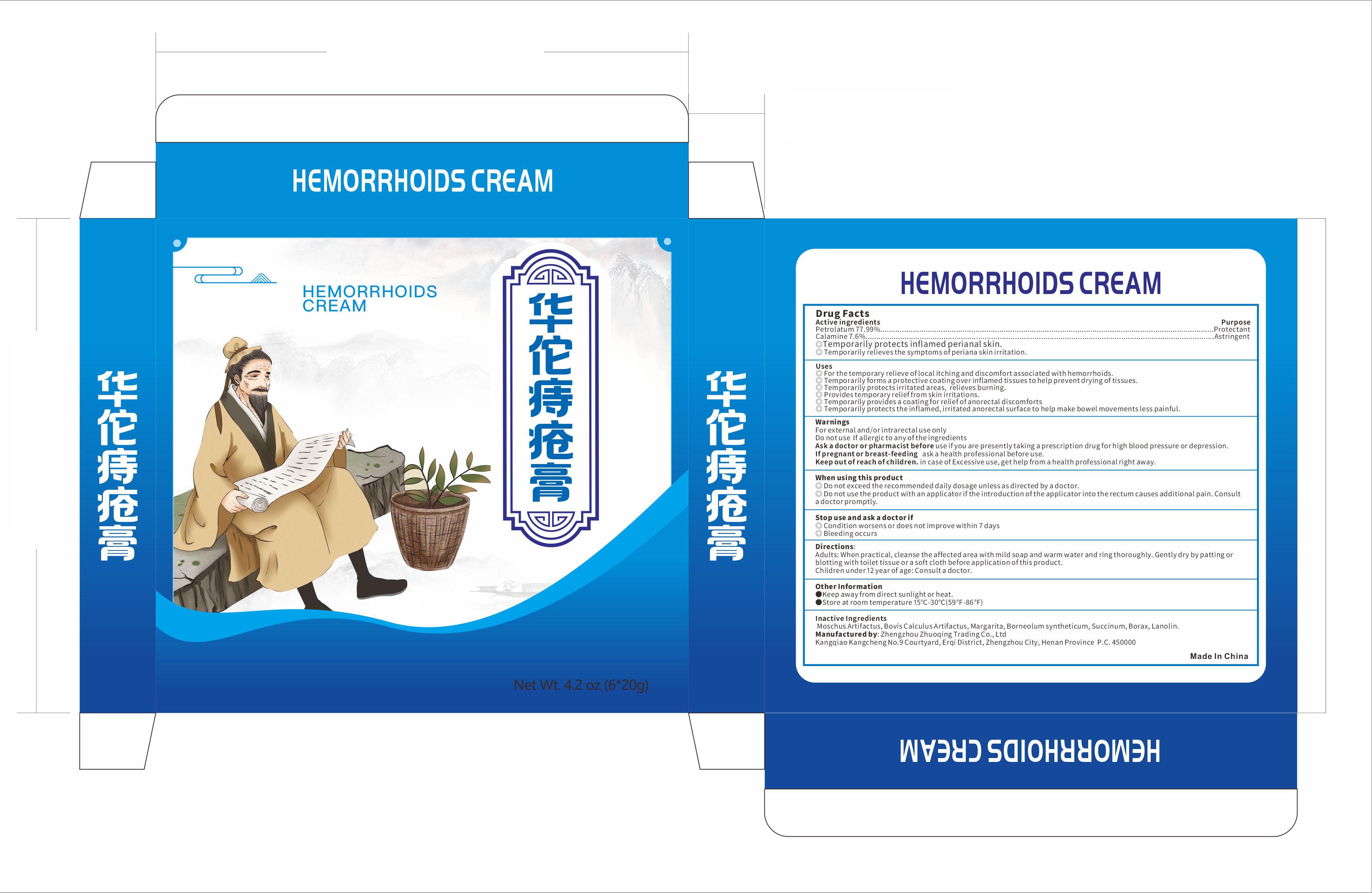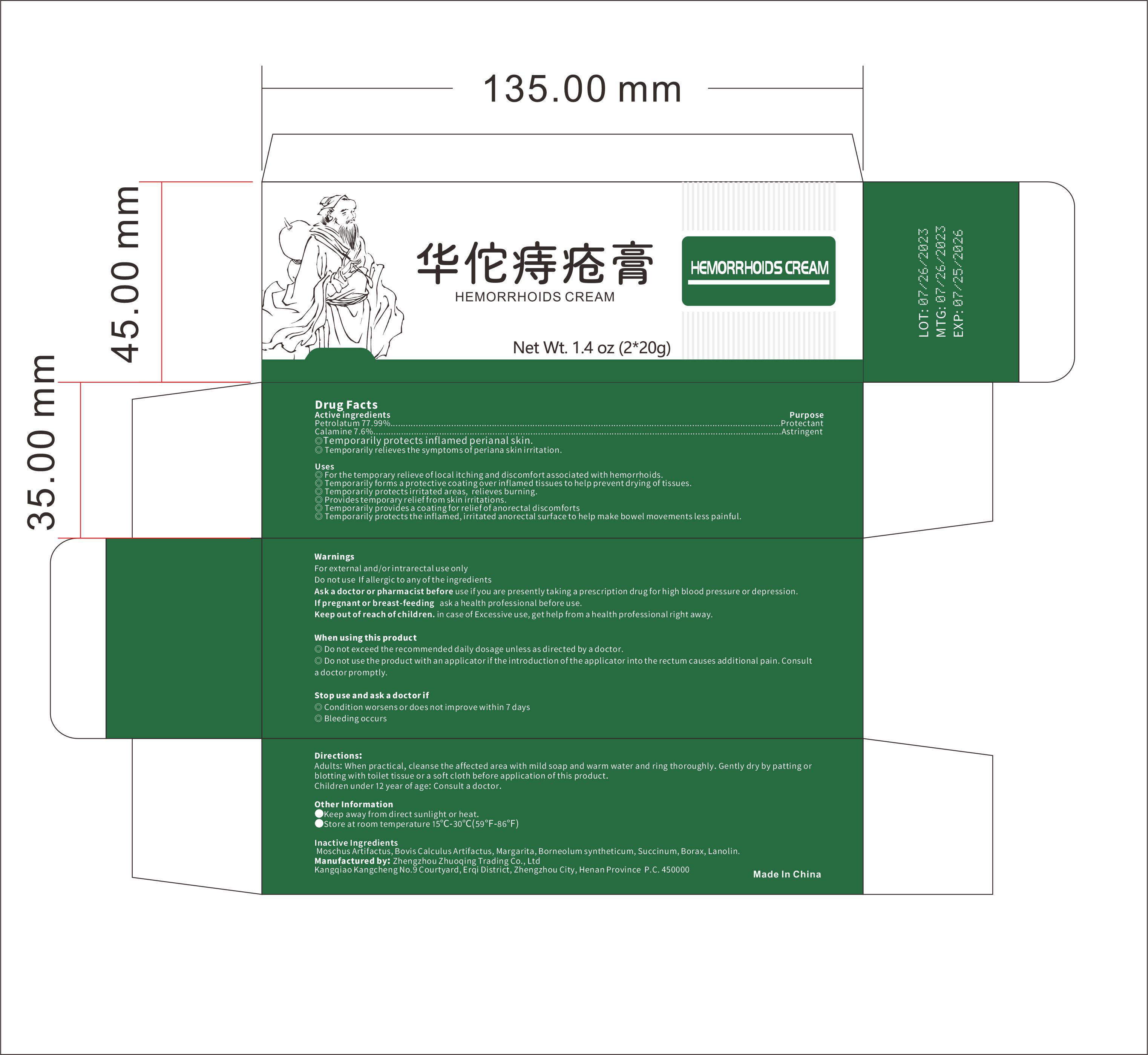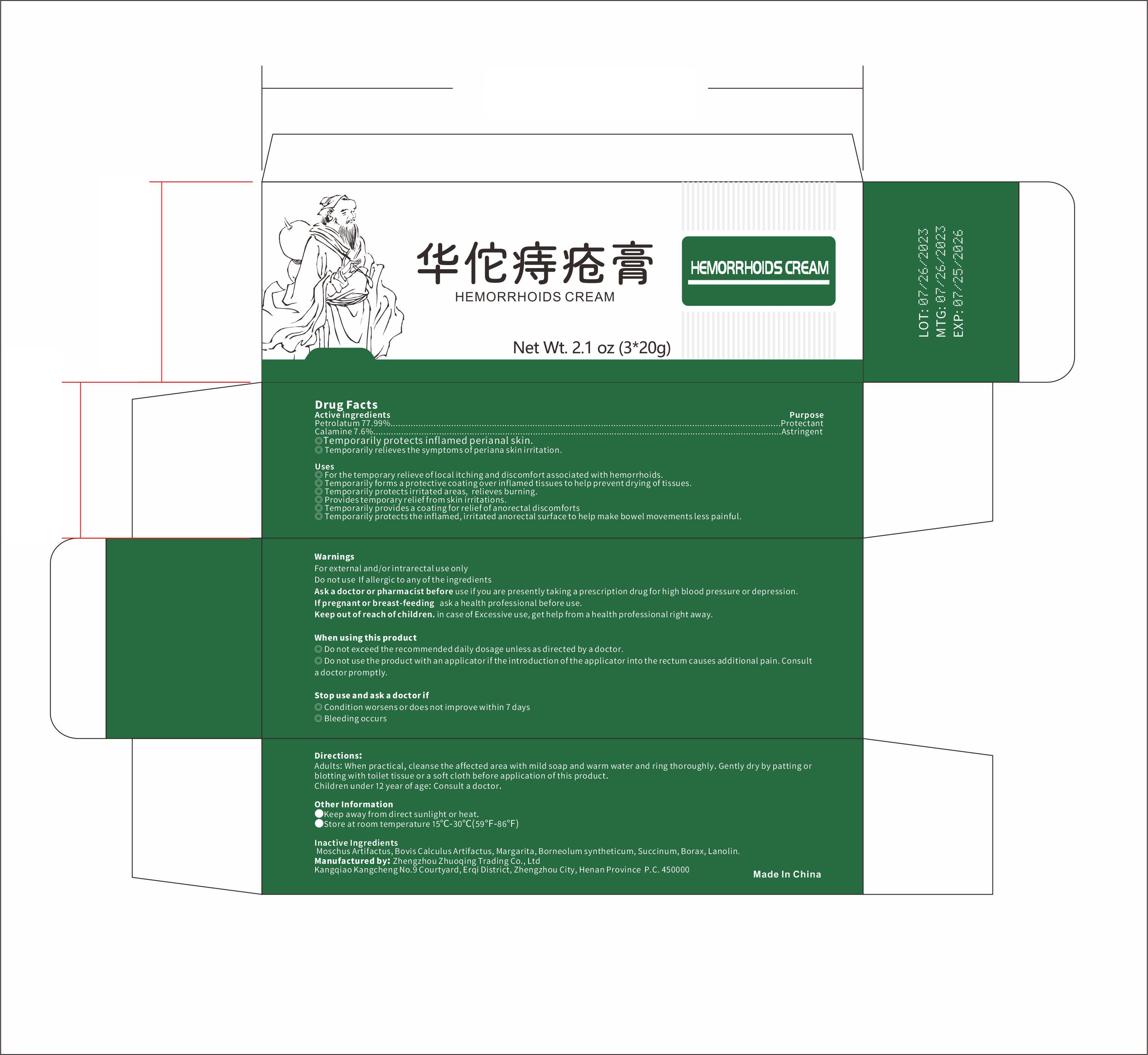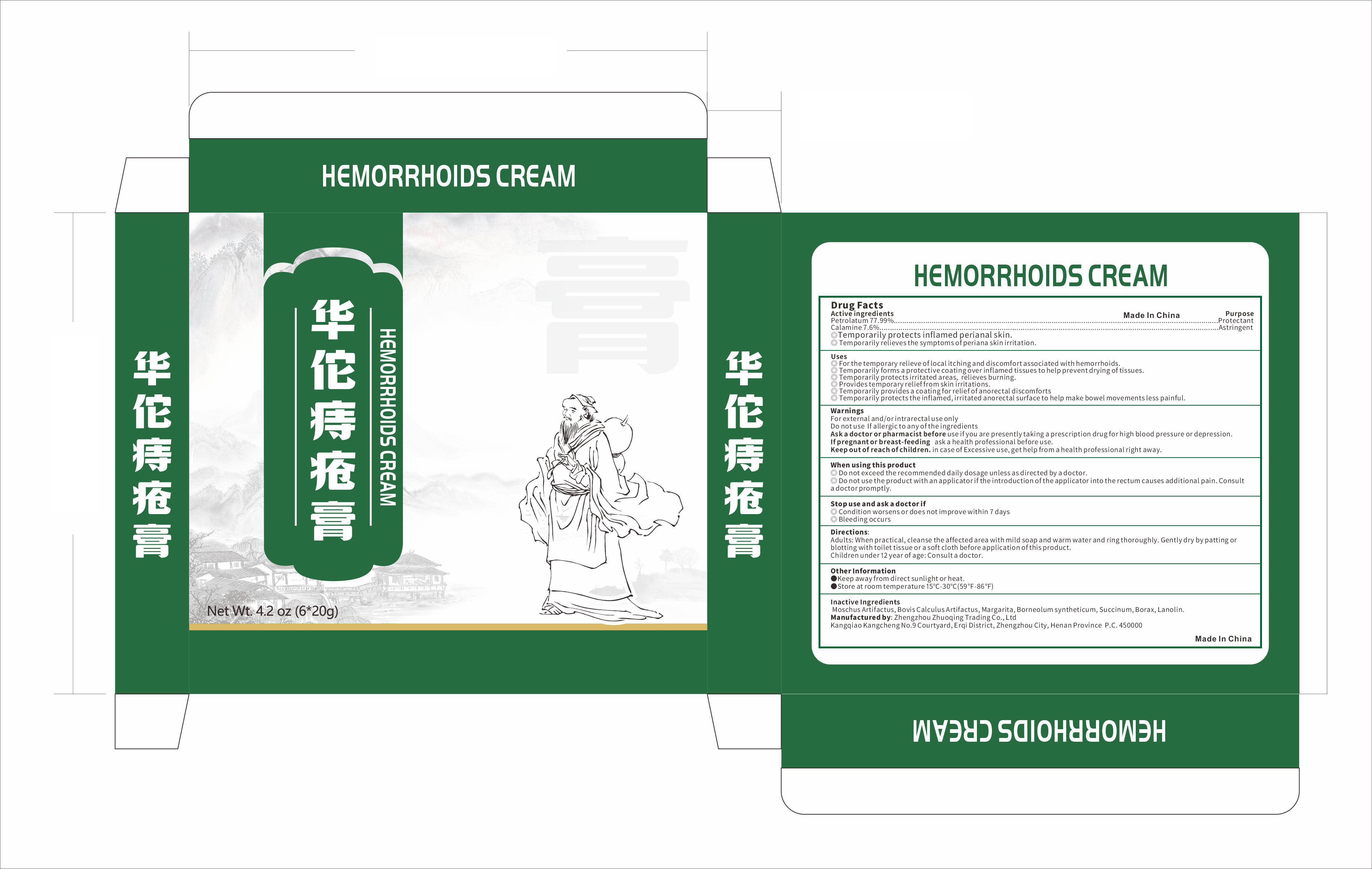 DRUG LABEL: HEMORRHOID
NDC: 83632-002 | Form: CREAM
Manufacturer: Zhengzhou Zhuoqing Trading Co., Ltd.
Category: otc | Type: HUMAN OTC DRUG LABEL
Date: 20231020

ACTIVE INGREDIENTS: ZINC OXIDE 7.6 g/100 g; PETROLATUM 77.99 g/100 g
INACTIVE INGREDIENTS: SODIUM BORATE; BORNEOL; LANOLIN; MICA; BOS TAURUS GALLSTONE; AMBER; MOSCHUS MOSCHIFERUS MUSK SAC RESIN

Active ingredients

Petrolatum 77.99%

Calamine 7.6%

PURPOSE

Protectant

Astringent

Temporarily protects inflamed perianal skin.

Temporarily relieves the symptoms of periana skin irritation

Uses

For the temporary relieve of local itching and discomfort associated with hemorrhoids.

Temporarily forms a protective coating over inflamed tissues to help prevent drying of tissues.

Temporarily protects irritated areas , relieves burning.

Provides temporary relief from skin irritations.

Temporarily provides a coating for relief of anorectal discomforts.

Temporarily protects the inflamed , irritated anorectal surface to help make bowel movements less painful

WARNINGS

For external and / or intrarectal use only

Ask a doctor or pharmacist before use if you are presently taking a prescription drug

Do not use If allergic to any of the ingredients.

Do not use the product with an applicator if the introduction of the applicator into the rectum causes additional pain Consult a doctor promptly

When usina this product

Do not exceed the recommended daily dosage unless as directed by a doctor.

Do not use If allergic to any of the ingredients

Do not use the product with an applicator if the introduction of the applicator into the rectum causes additional pain. Consult a doctor promptly

Stop use and ask a doctor if

Condition worsens or does not improve within 7 days

Bleeding occurs

Keep out of reach of children , in case of Excessive use , get help from a health professional right away

Directions

Adults : When practical , cleanse the affected area with mild soap and warm water and ring thoroughly . Gently dry by atting or blotting with toilet tissue or a soft cloth before application of this product .Children under 12 year of age : Consult a doctor

Other Information

Keep away from direct sunlight or heat.

Store at room temperature 15°C-30°C (59F-86F)

Inactive Ingredients

Moschus Artifactus , Bovis Calculus Artifactus , Margarita , Borneolum syntheticum , Succinum , Borax , Lanolin